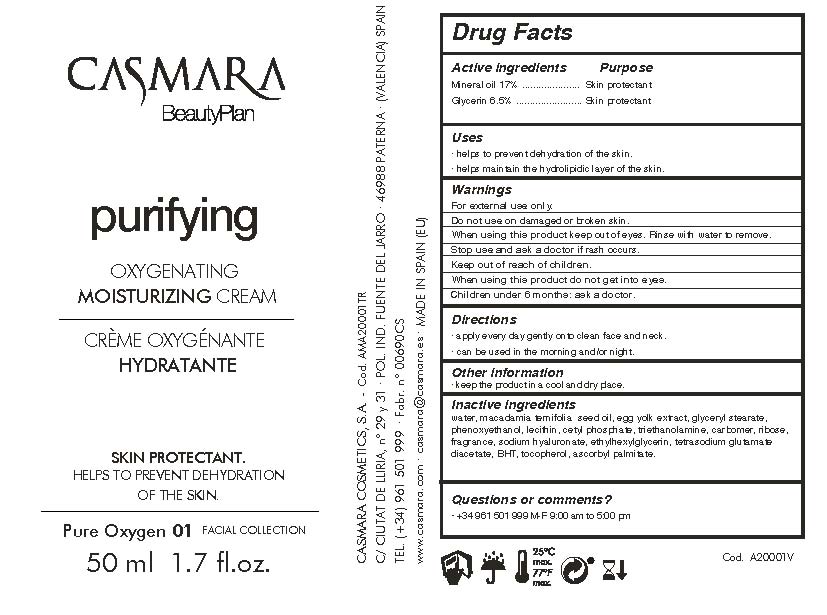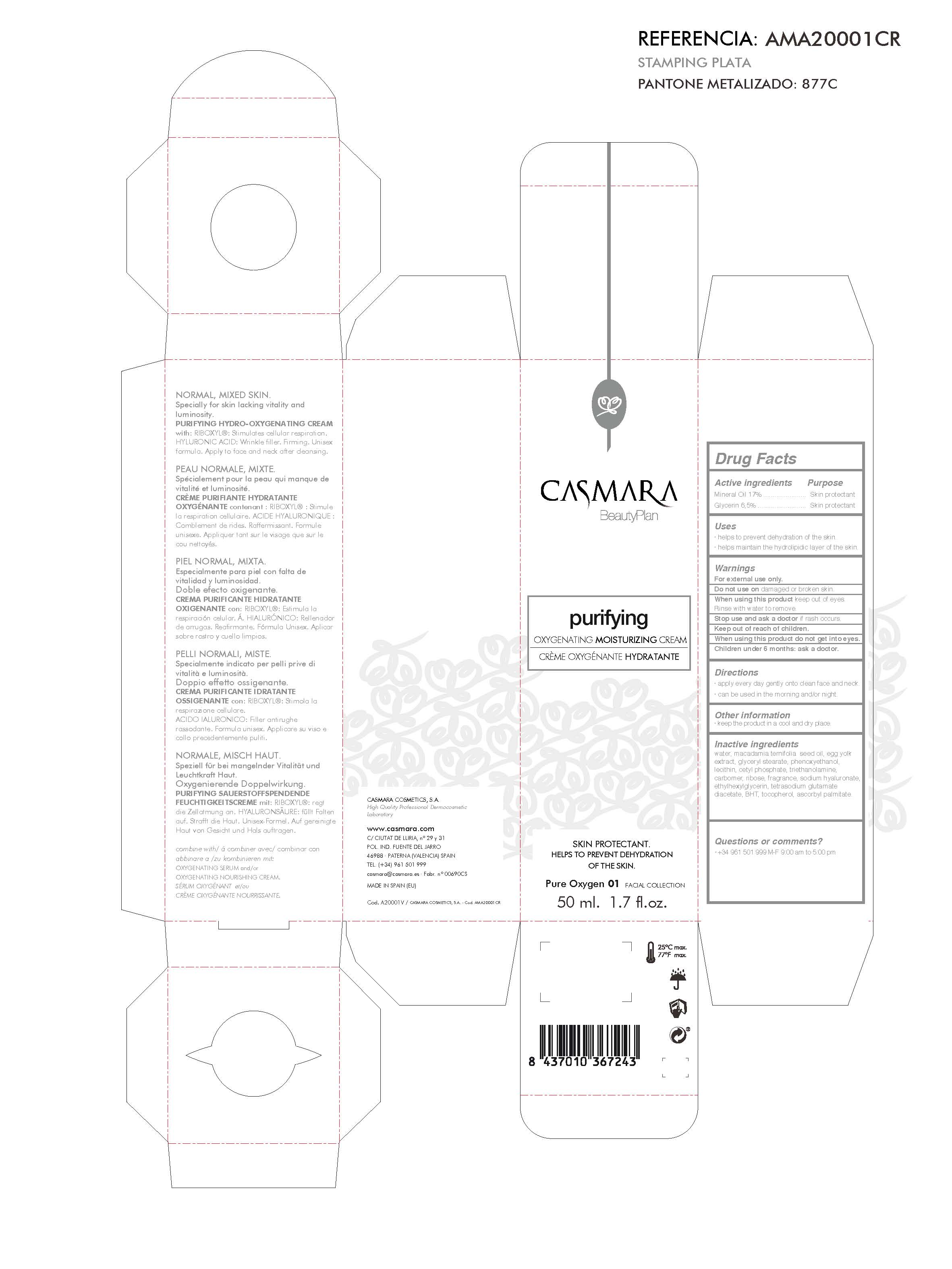 DRUG LABEL: Purifying Oxygenating Moisturizing Cream
NDC: 20151-083 | Form: CREAM
Manufacturer: Casmara Cosmetics, SA
Category: otc | Type: HUMAN OTC DRUG LABEL
Date: 20170222

ACTIVE INGREDIENTS: GLYCERIN 6.5 mg/1 mL; MINERAL OIL 17 mg/1 mL
INACTIVE INGREDIENTS: EGG YOLK 2 mg/1 mL; GLYCERYL STEARATE SE 2 mg/1 mL; PHENOXYETHANOL 0.9 mg/1 mL; LECITHIN, SOYBEAN 0.62 mg/1 mL; CETYL PHOSPHATE 0.625 mg/1 mL; MACADAMIA OIL 4.99 mg/1 mL; TROLAMINE 0.6 mg/1 mL; CARBOXYPOLYMETHYLENE 0.45 mg/1 mL; RIBOSE, D- 0.2 mg/1 mL; PEG-9 DIGLYCIDYL ETHER/SODIUM HYALURONATE CROSSPOLYMER 0.1 mg/1 mL; ETHYLHEXYLGLYCERIN 0.1 mg/1 mL; TETRASODIUM GLUTAMATE DIACETATE 0.094 mg/1 mL; TOCOPHEROL 0.002 mg/1 mL; ASCORBYL PALMITATE 0.0005 mg/1 mL; BUTYLATED HYDROXYTOLUENE 0.011 mg/1 mL; WATER 63.59 mg/1 mL

PURIFYING OXYGENATING MOISTURIZING CREAM

DIRECTIONS

. apply every day gently onto clean face and neck

. can be used in the morning and/or night.

ACTIVE INGREDIENTS PURPOSE

Mineral Oil 20%..................Skin Protectant

Glycerin 6.5%..................... Skin Protectant

WARNINGS

Children under 6 months: ask a doctor

WARNINGS

Keep out of reach of children

USES

. helps to prevent dehydration of the skin

. helps maintain the hydrolipidic layer of the skin

DIRECTIONS

. apply every day gently onto clean face and neck

. can be used in the morning and/or night.

WARNINGS

For external use only.

Do not use on damaged or broken skin.

When using this product keep out of eyes. Rinse with water to remove.

Stop use and ask a doctor if rash occurs.

Keep out of reach of children.

When using this product do not get into eyes.

Children under 6 months: ask a doctor

OTHER INFORMATION

keep the product in a cool and dry place.

INACTIVE INGREDIENTS

water, peg-40 castor oil, phenoxyethanol, sodium polyacrylate, betaine, cyclopentasiloxane, trideceth-6, ribose, fragrance, ethylhexylglycerin, tetrasodium glutamate diacetate, peg/ppg- 18/18 dimethicone, perfluorodecalin, simmondsia chinensis (jojoba) seed oil, ceramide np, sucrose palmitate, xanthan gum, sodium benzoate, potassium sorbate.

QUESTIONS OR COMMENTS?

+ 34 961 501 999 M-F 9:00 am to 5:00 pm